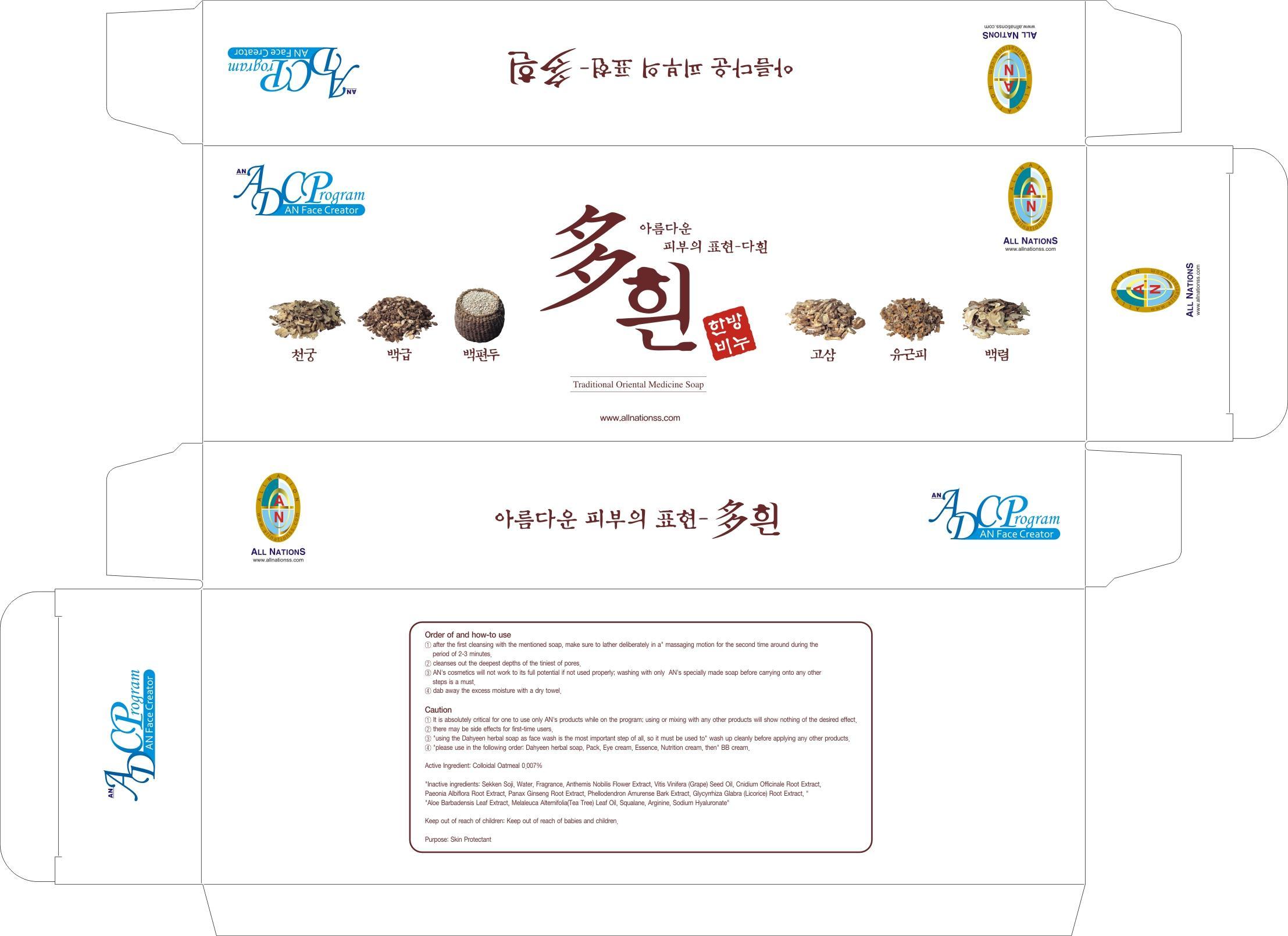 DRUG LABEL: HERBAL DAHUIN BEAUTY
NDC: 69153-010 | Form: SOAP
Manufacturer: AN Co Ltd.
Category: otc | Type: HUMAN OTC DRUG LABEL
Date: 20191218

ACTIVE INGREDIENTS: OATMEAL 0.007 g/3 1
INACTIVE INGREDIENTS: Water; GRAPE SEED OIL

ACTIVE INGREDIENT

Active Ingredient: Colloidal Oatmeal 0.007%

INACTIVE INGREDIENT

Inactive ingredients: Sekken Soji, Water, Fragrance, Anthemis Nobilis Flower Extract, Vitis Vinifera (Grape) Seed Oil, Cnidium Officinale Root Extract, Paeonia Albiflora Root Extract, Panax Ginseng Root Extract, Phellodendron Amurense Bark Extract, Glycyrrhiza Glabra (Licorice) Root Extract, Aloe Barbadensis Leaf Extract, Melaleuca Alternifolia(Tea Tree) Leaf Oil, Squalane, Arginine, Sodium Hyaluronate

PURPOSE

Purpose: Skin Protectant

Caution

1. It is absolutely critical for one to use only AN's products while on the program; using or mixing with any other products will show nothing of the desired effect.
2. There may be side effects for first-time users.
3. Using the Dahyeen herbal soap as face wash is the most important step of all, so it must be used to wash up cleanly before applying any other products.
4. please use in the following order: Dahyeen herbal soap, Pack, Eye cream, Essence, Nutrition cream, then BB cream.

Keep out of reach of children: Keep out of reach of babies and children.

INDICATIONS & USAGE

Order of and how-to use
1. After the first cleansing with the mentioned soap, make sure to lather deliberately in a massaging motion for the second time around during the period of 2-3 minutes.
2. Cleanses out the deepest depths of the tiniest of pores.
3. AN's cosmetics will not work to its full potential if not used properly; washing with only AN's specially made soap before carrying onto any other steps is a must.
4. Dab away the excess moisture with a dry towel.

DOSAGE & ADMINISTRATION

Order of and how-to use
1. After the first cleansing with the mentioned soap, make sure to lather deliberately in a massaging motion for the second time around during the period of 2-3 minutes.
2. Cleanses out the deepest depths of the tiniest of pores.
3. AN's cosmetics will not work to its full potential if not used properly; washing with only AN's specially made soap before carrying onto any other steps is a must.
4. Dab away the excess moisture with a dry towel.